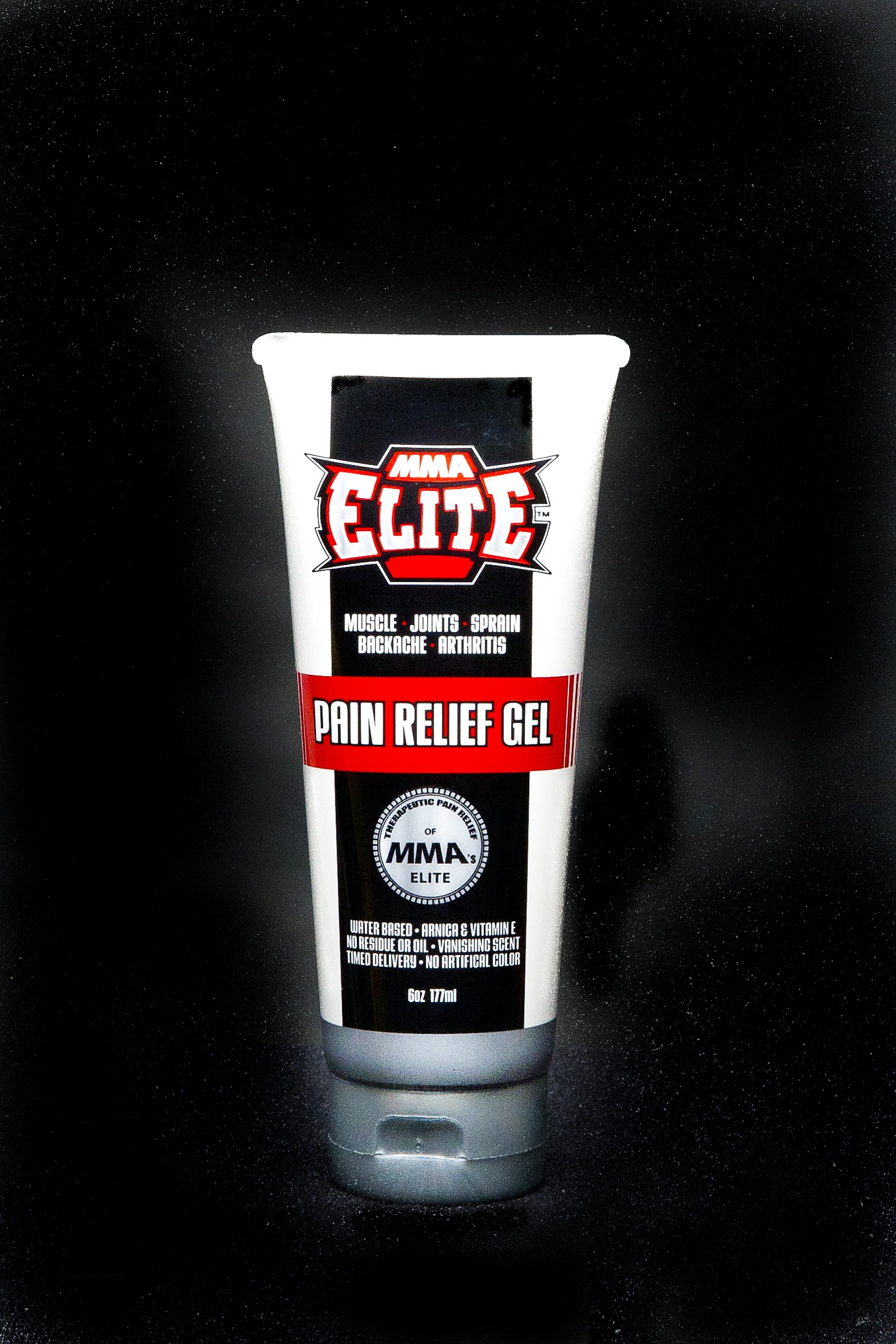 DRUG LABEL: MMA Elite Pain Relief
NDC: 24462-200 | Form: GEL
Manufacturer: MMA Pain Relief Gel, LLC
Category: otc | Type: HUMAN OTC DRUG LABEL
Date: 20111118

ACTIVE INGREDIENTS: menthol 5 g/100 g; CAMPHOR (NATURAL) 5 g/100 g
INACTIVE INGREDIENTS: arnica montana; water; Witch hazel; ISOPROPYL ALCOHOL

DRUG FACTS

Active Ingredients Purpose

Camphor (5%) External Analgesic
Menthol (5%) External Analgesic

Uses:
temporary relief of minor aches and pains of muscles
and joints due to:
* simple backache
* arthritis
* sprains
* strains
* bruises

Warnings:
* for external use only
* do not apply to open wounds or damaged skin
* do not bandage tightly
* avoid contact with eyes
* Keep out of reach of children. if swallowed, get medical help or contact a Poison Control Center immediately
* if condition worsens, or if symptoms persist for more than 7 days or clear up and occur again within a few days, discontinue use of this product and consult a physician
* Pregnancy-breast feeding warning: if pregnant or breast feeding, ask a health professional before use

Inactive Ingredients:
distilled water, hamamelis virginiana (witch hazel extract),
isopropyl alcohol, arnica Montana, oleyl alcohol and
zanthoxylum alatum (scezhuan pepper), Bio-saccharide
Gum -1, glycerin, ammonium acryloyldimethyltaurate/VP
copolymer, beta cyclodextrin, menthol, potassium hydroxide,
mannitol, cellulose chromium, hydroxide green, tocopheryl
acetate (vitamin E), hydroxypropyl methycellulose

Directions:
For best results, apply generously to affected and surrounding areas. Use 1 layer for minor pain, 2 for medium and 3 layers for severs symptoms. Rub in well. Allow to dry between layers (usually just 2-3 minutes). Repeat process up to 4 times daily. For adults and children 2 years and older. For children under 2 years of age, consult a doctor.

Directions:
For best results, apply generously to affected and surrounding areas. Use 1 layer for minor pain, 2 for medium and 3 layers for severs symptoms. Rub in well. Allow to dry between layers (usually just 2-3 minutes). Repeat process up to 4 times daily. For adults and children 2 years and older. For children under 2 years of age, consult a doctor.

Uses:
temporary relief of minor aches and pains of muscles
and joints due to:
* simple backache
* arthritis
* sprains
* strains
* bruises

Warnings:
* for external use only
* do not apply to open wounds or damaged skin
* do not bandage tightly
* avoid contact with eyes
* Keep out of reach of children. if swallowed, get medical help or contact a Poison Control Center immediately
* if condition worsens, or if symptoms persist for more than 7 days or clear up and occur again within a few days, discontinue use of this product and consult a physician
* Pregnancy-breast feeding warning: if pregnant or breast feeding, ask a health professional before use

PACKAGE LABEL

An image/jpeg of the container label is included in this section.

ID: MM1